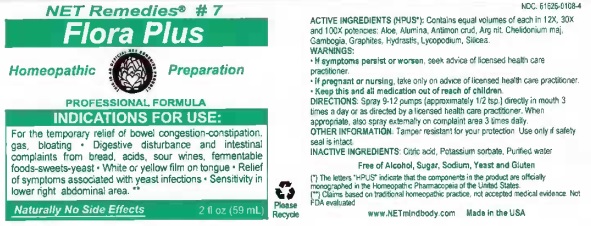 DRUG LABEL: Flora Plus
NDC: 61626-0108 | Form: LIQUID
Manufacturer: NET Remedies
Category: homeopathic | Type: HUMAN OTC DRUG LABEL
Date: 20210121

ACTIVE INGREDIENTS: ALOE VERA LEAF 12 [hp_X]/59.1 mL; ALUMINUM OXIDE 12 [hp_X]/59.1 mL; ANTIMONY TRISULFIDE 12 [hp_X]/59.1 mL; SILVER NITRATE 12 [hp_X]/59.1 mL; CHELIDONIUM MAJUS 12 [hp_X]/59.1 mL; GAMBOGE 12 [hp_X]/59.1 mL; GRAPHITE 12 [hp_X]/59.1 mL; GOLDENSEAL 12 [hp_X]/59.1 mL; LYCOPODIUM CLAVATUM SPORE 12 [hp_X]/59.1 mL; SILICON DIOXIDE 12 [hp_X]/59.1 mL
INACTIVE INGREDIENTS: CITRIC ACID MONOHYDRATE; POTASSIUM SORBATE; WATER

Flora Plus

ACTIVE INGREDIENT

ACTIVE INGREDIENTS (HPUS*): Contains equal volumes of each in 12X, 30X, and 100X potencies: Aloe, Alumina, Antimon crud, Chelidonium maj, Gambogia, Graphites, Hydrastis, Lycopodium, Silicea.

)*) The letters "HPUS" indicate that the components in the product are officially monographed in the Homeopathic Pharmacopeia of the United States.

(**) Claims based on traditional homeopathic practice, not accepted medical evidence. Not FDA evaluated.

INDICATIONS AND USAGE

INDICATIONS FOR USE: For temporary relief of bowel congestions-constipation, gas, bloating • Digestive disturbance and intestinal complaints from bread, acids, sour wines, fermentable foods-sweets-yeast • White or yellow film on tongue • Relief of symptoms associated with yeast infections • Sensitivity in lower right abdominal area. **

WARNINGS

WARNINGS:• If symptoms persist or worsen, seek advice of licensed health care practicioner.

• If pregnant or nursing, take only on advice of licensed health care practicioner.

• Keep this and all medication out of reach of children.

KEEP OUT OF REACH OF CHILDREN

• Keep this and all medication out of reach of children.

DOSAGE AND ADMINISTRATION

DIRECTIONS: Spray 9-12 pumps (approximately 1/2 tsp.) directly in mouth 3 times a day or as directed by a licensed health care practicioner. When appropriate, also spray externally on complaint area 3 times daily.

INACTIVE INGREDIENTS: Citric acid, Potassium sorbate, Purified water.

Free of Alcohol, Sugar, Sodium, Yeast and Gluten

QUESTIONS

www.NETmindbody.com

Made in the USA.

PACKAGE LABEL

NET Remedies #7

Flora Plus

Homeopathic Preparation

PROFESSIONAL FORMULA

PURPOSE

INDICATIONS FOR USE: For temporary relief of bowel congestions-constipation, gas, bloating • Digestive disturbance and intestinal complaints from bread, acids, sour wines, fermentable foods-sweets-yeast • White or yellow film on tongue • Relief of symptoms associated with yeast infections • Sensitivity in lower right abdominal area. **